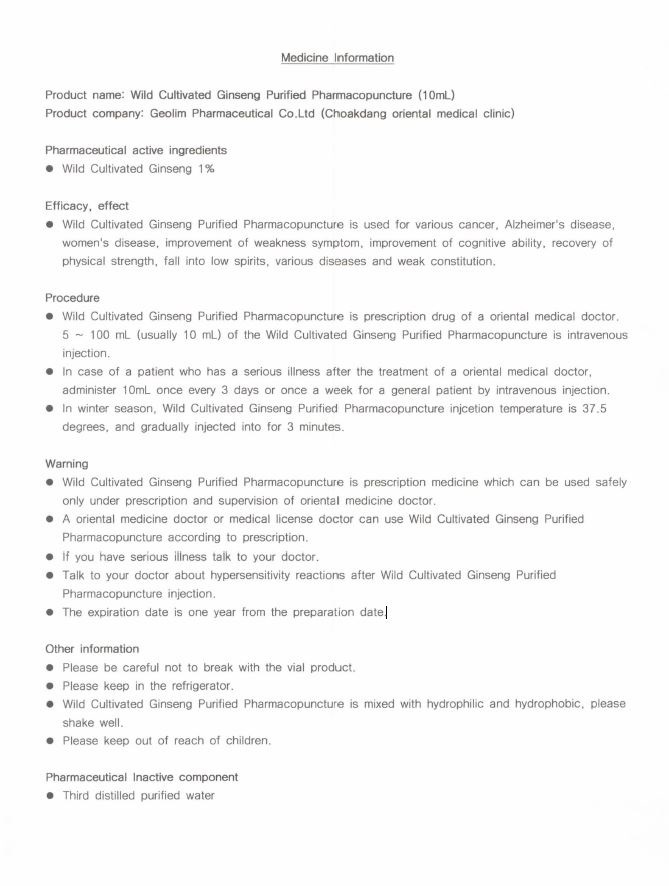 DRUG LABEL: Wild Cultivated Ginseng Purified Pharmacopuncture
NDC: 71291-0012 | Form: LIQUID
Manufacturer: GEOLIM Pharmaceutical CO., Ltd. (Busan Branch)
Category: otc | Type: HUMAN OTC DRUG LABEL
Date: 20221113

ACTIVE INGREDIENTS: ASIAN GINSENG 1 g/100 mL
INACTIVE INGREDIENTS: WATER

Drug Facts

ACTIVE INGREDIENT

Wild Cultivated Ginseng 1%

INACTIVE INGREDIENT

Third distilled purified water

PURPOSE

Wild Cultivated Ginseng Purified Pharmacopuncture is used for various cancer, Alzheimer's disease, women's disease, improvement of weakness symptom, improvement of cognitive ability, recovery of physical strength, fall into low spirits, various diseases and weak constitution.

keep out or reach of the children

INDICATIONS AND USAGE

• Wild Cultivated Ginseng Purified Pharmacopuncture is prescription drug of a oriental medical doctor.
5 - 100 ml (usually 10 ml) of the Wild Cultivated Ginseng Purified Pharmacopuncture is intravenous
injection.
• In case of a patient who has a serious illness after the treatment of a oriental medical doctor,
administer 1 Oml once every 3 days or once a week for a general patient by intravenous injection.
• In winter season, Wild Cultivated Ginseng Purified Pharmacopuncture injcetion temperature is 37.5
degrees, and gradually injected into for 3 minutes.

WARNINGS

• Wild Cultivated Ginseng Purified Pharmacopuncture is prescription medicine which can be used safely
only under prescription and supervision of oriental medicine doctor.
• A oriental medicine doctor or medical license doctor can use Wild Cultivated Ginseng Purified
Pharmacopuncture according to prescription.
• If you have serious illness talk to your doctor.
• Talk to your doctor about hypersensitivity reactions after Wild Cultivated Ginseng Purified
Pharmacopuncture injection.
• The expiration date is one year from the preparation date.

DOSAGE AND ADMINISTRATION

for external use only